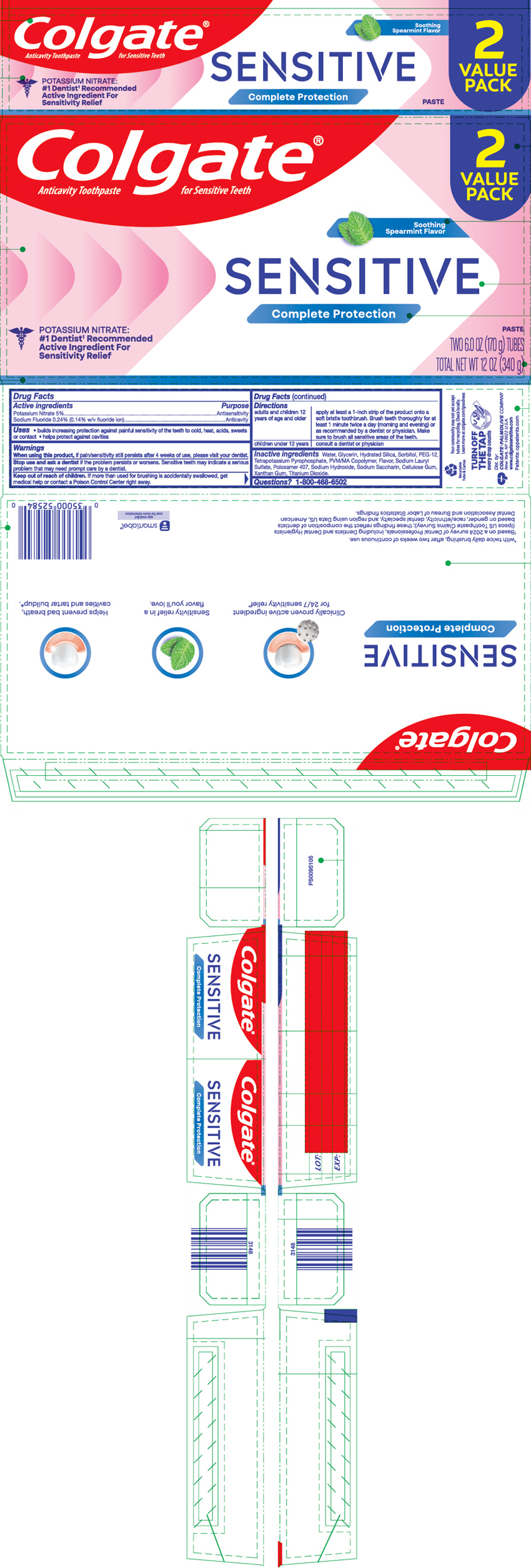 DRUG LABEL: Colgate Sensitive Complete Protection
NDC: 35000-132 | Form: PASTE, DENTIFRICE
Manufacturer: Colgate-Palmolive Company
Category: otc | Type: HUMAN OTC DRUG LABEL
Date: 20260122

ACTIVE INGREDIENTS: POTASSIUM NITRATE 50 mg/1 g; SODIUM FLUORIDE 1.1 mg/1 g
INACTIVE INGREDIENTS: WATER; GLYCERIN; HYDRATED SILICA; SORBITOL; POLYETHYLENE GLYCOL 600; POTASSIUM PYROPHOSPHATE; METHYL VINYL ETHER AND MALEIC ACID COPOLYMER (1750000 WAMW); SODIUM LAURYL SULFATE; POLOXAMER 407; SODIUM HYDROXIDE; SACCHARIN SODIUM; CARBOXYMETHYLCELLULOSE SODIUM, UNSPECIFIED; XANTHAN GUM; TITANIUM DIOXIDE

Colgate® Sensitive Complete Protection

Drug Facts

ACTIVE INGREDIENT

Active ingredients | Purpose
Potassium Nitrate 5% | Antisensitivity
Sodium Fluoride 0.24% (0.14% w/v fluoride ion) | Anticavity

Uses

- builds increasing protection against painful sensitivity of the teeth to cold, heat, acids, sweets or contact
- helps protect against cavities

Warnings

When using this product, if pain/sensitivity still persists after 4 weeks of use, please visit your dentist.

Stop use and ask a dentist if the problem persists or worsens. Sensitive teeth may indicate a serious problem that may need prompt care by a dentist.

Keep out of reach of children. If more than used for brushing is accidentally swallowed, get medical help or contact a Poison Control Center right away.

Directions

adults and children 12 years of age and older | apply at least a 1-inch strip of the product onto a soft bristle toothbrush. Brush teeth thoroughly for at least 1 minute twice a day (morning and evening) or as recommended by a dentist or physician. Make sure to brush all sensitive areas of the teeth.
children under 12 years | consult a dentist or physician

Inactive ingredients

Water, Glycerin, Hydrated Silica, Sorbitol, PEG-12, Tetrapotassium Pyrophosphate, PVM/MA Copolymer, Flavor, Sodium Lauryl Sulfate, Poloxamer 407, Sodium Hydroxide, Sodium Saccharin, Cellulose Gum, Xanthan Gum, Titanium Dioxide.

Questions?

1-800-468-6502

Dist. by:
COLGATE-PALMOLIVE COMPANY
New York, NY 10022 U.S.A.

PRINCIPAL DISPLAY PANEL - 170 g Tube Carton

Colgate®
Anticavity Toothpaste for Sensitive Teeth

2
VALUE
PACK

Soothing
Spearmint Flavor

SENSITIVE
Complete Protection

POTASSIUM NITRATE:
#1 Dentist^1 Recommended
Active Ingredient For
Sensitivity Relief

PASTE

TWO 6.0 OZ (170 g) TUBES

TOTAL NET WT 12 OZ (340 g)